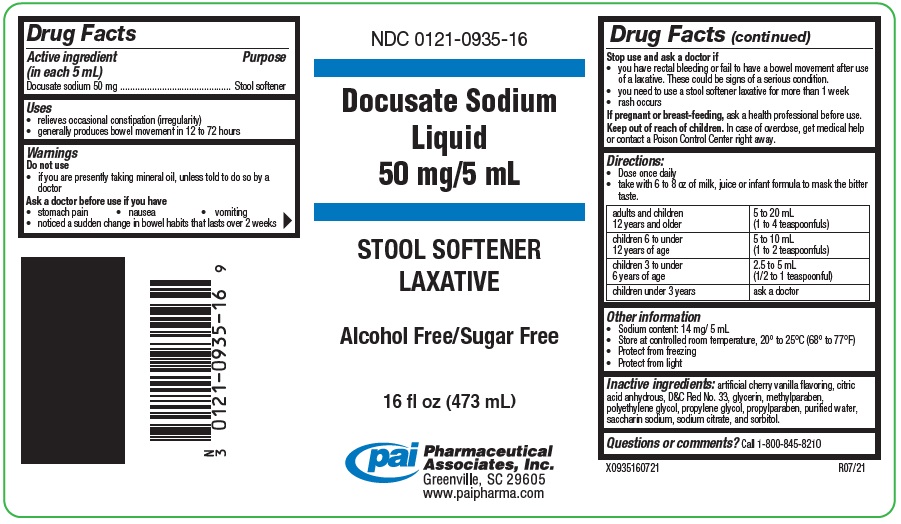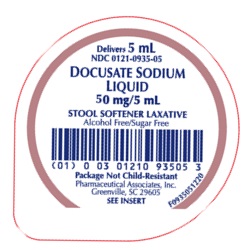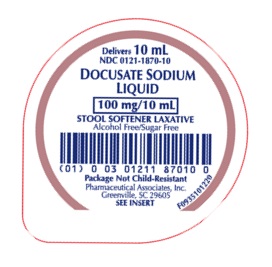 DRUG LABEL: Docusate Sodium
NDC: 0121-0935 | Form: LIQUID
Manufacturer: PAI Holdings, LLC dba PAI Pharma
Category: otc | Type: HUMAN OTC DRUG LABEL
Date: 20250206

ACTIVE INGREDIENTS: DOCUSATE SODIUM 50 mg/5 mL
INACTIVE INGREDIENTS: ANHYDROUS CITRIC ACID; D&C RED NO. 33; GLYCERIN; METHYLPARABEN; PROPYLENE GLYCOL; PROPYLPARABEN; WATER; SODIUM CITRATE; SACCHARIN SODIUM; SORBITOL SOLUTION

Docusate Sodium

Drug Facts

Active ingredient (in each 5 mL)

Docusate sodium 50 mg

Purpose

Stool softener

Uses

- relieves occasional constipation (irregularity)
- generally produces bowel movement in 12 to 72 hours

Warnings

Do not use

- if you are presently taking mineral oil, unless told to do so by a doctor

Ask a doctor before use if you have

- stomach pain
- nausea
- vomiting
- noticed a sudden change in bowel habits that lasts over 2 weeks

Stop use and ask a doctor if

- you have rectal bleeding or fail to have a bowel movement after use of a laxative. These could be signs of a serious condition.
- you need to use a stool softener laxative for more than 1 week
- rash occurs

PREGNANCY OR BREAST FEEDING

If pregnant or breast-feeding, ask a health professional before use.

Keep out of reach of children. In case of overdose, get medical help or contact a Poison Control Center right away.

Directions

- Dose once daily
- take with 6 to 8 oz of milk, juice or infant formula to mask the bitter taste.

adults and children 12 years and older | 5 to 20 mL (1 to 4 teaspoonfuls)
children 6 to under 12 years of age | 5 to 10 mL (1 to 2 teaspoonfuls)
children 3 to under 6 years of age | 2.5 to 5 mL (1/2 to 1 teaspoonful)
children under 3 years | ask a doctor

Other information

• Sodium content: 14 mg/ 5 mL
• Store at controlled room temperature, 20° to 25°C (68° to 77°F)
• Protect from freezing
• Protect from light
• Clear pink to purple-pink colored, cherry flavored liquid supplied in the following:

NDC 0121-0935-16: 16 fl oz (473 mL) bottle
NDC 0121-0935-05: 5 mL unit dose cup, in a tray of ten cups.
NDC 0121-1870-10: 10 mL unit dose cup, in a tray of ten cups.

Inactive ingredients

artificial cherry vanilla flavoring, citric acid anhydrous, D&C Red No. 33, glycerin, methylparaben, polyethylene glycol, propylene glycol, propylparaben, purified water, saccharin sodium, sodium citrate, and sorbitol.

Questions or comments?

Call 1-800-845-8210

MANUFACTURED BY

Pharmaceutical Associates, Inc.

Greenville, SC 29605

R12/20

PRINCIPAL DISPLAY PANEL - 16 fl oz (473 ML)

NDC 0121-0935-16

Docusate Sodium Liquid

50 mg/5 mL

STOOL SOFTENER LAXATIVE

Alcohol Free/Sugar Free

16 fl oz (473 mL)

Pharmaceutical Associates, Inc.

Greenville, SC 29605

X0935160721 R07/21

PRINCIPAL DISPLAY PANEL - 5 mL Cup LIdding

NDC 0121-0935-05

Docusate Sodium Liquid

50 mg/5 mL

STOOL SOFTENER LAXATIVE

Alcohol Free/Sugar Free

Package Not Child-Resistant

Pharmaceutical Associates, Inc.

Greenville, SC 29605

PRINCIPAL DISPLAY PANEL - 10 mL Cup Lidding

NDC 0121-1870-10

Docusate Sodium Liquid

100 mg/10 mL

STOOL SOFTENER LAXATIVE

Alcohol Free/Sugar Free

Package Not Child-Resistant

Pharmaceutical Associates, Inc.

Greenville, SC 29605